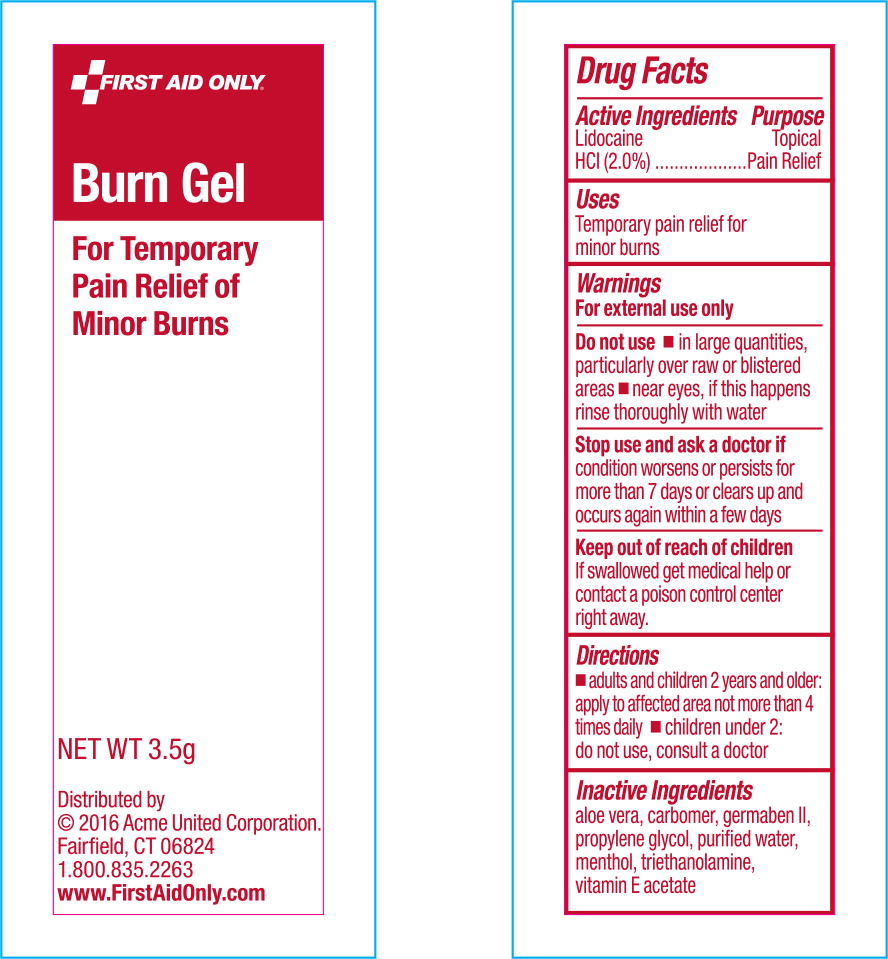 DRUG LABEL: Lidocaine Hydrochloride
NDC: 0924-5000 | Form: GEL
Manufacturer: Acme United Corporation
Category: otc | Type: HUMAN OTC DRUG LABEL
Date: 20160307

ACTIVE INGREDIENTS: Lidocaine Hydrochloride 20 mg/1 g
INACTIVE INGREDIENTS: aloe vera leaf; propylene glycol; diazolidinyl urea; water; menthol; .alpha.-tocopherol acetate; trolamine

Burn Gel
Pain Relief

Drug Facts

Active ingredients

Lidocaine HCl 2%

Purpose

Topical pain relief

Uses

Temporary pain relief of minor burns. For professional use only.

Warnings

For external use only. Keep out of reach of children.

If ingested, get medical help or contact a Poison Control Center directly

Do not use

- In large quantities, particularly over raw or blistered areas
- near eyes, if this happens rinse thoroughly with water

Stop use and ask doctor if

- the condition worsens or if symptoms persist for more than 7 days or clear up and occur again within a few days

Directions

Adults and children 2 years and over: apply to affected area not more than 3 to 4 times daily

Children under 2 years: do not use, consult a doctor

Other information

- store at room temperature (do not freeze)
- do not use any opened or torn packs

Inactive ingredients

aloe vera, carbomer, germaben II, menthol, propylene glycol, purified water, triethanolamine, Vitamin E acetate

Principal Display Panel - Pouch Label

FIRST AID ONLY®

Burn Gel

For Temporary
Pain Relief of
Minor Burns

NET WT 3.5g

Distributed by

© 2016 Acme United Corporation.

Fairfield, CT 06824

1.800.835.2263

www.FirstAidOnly.com